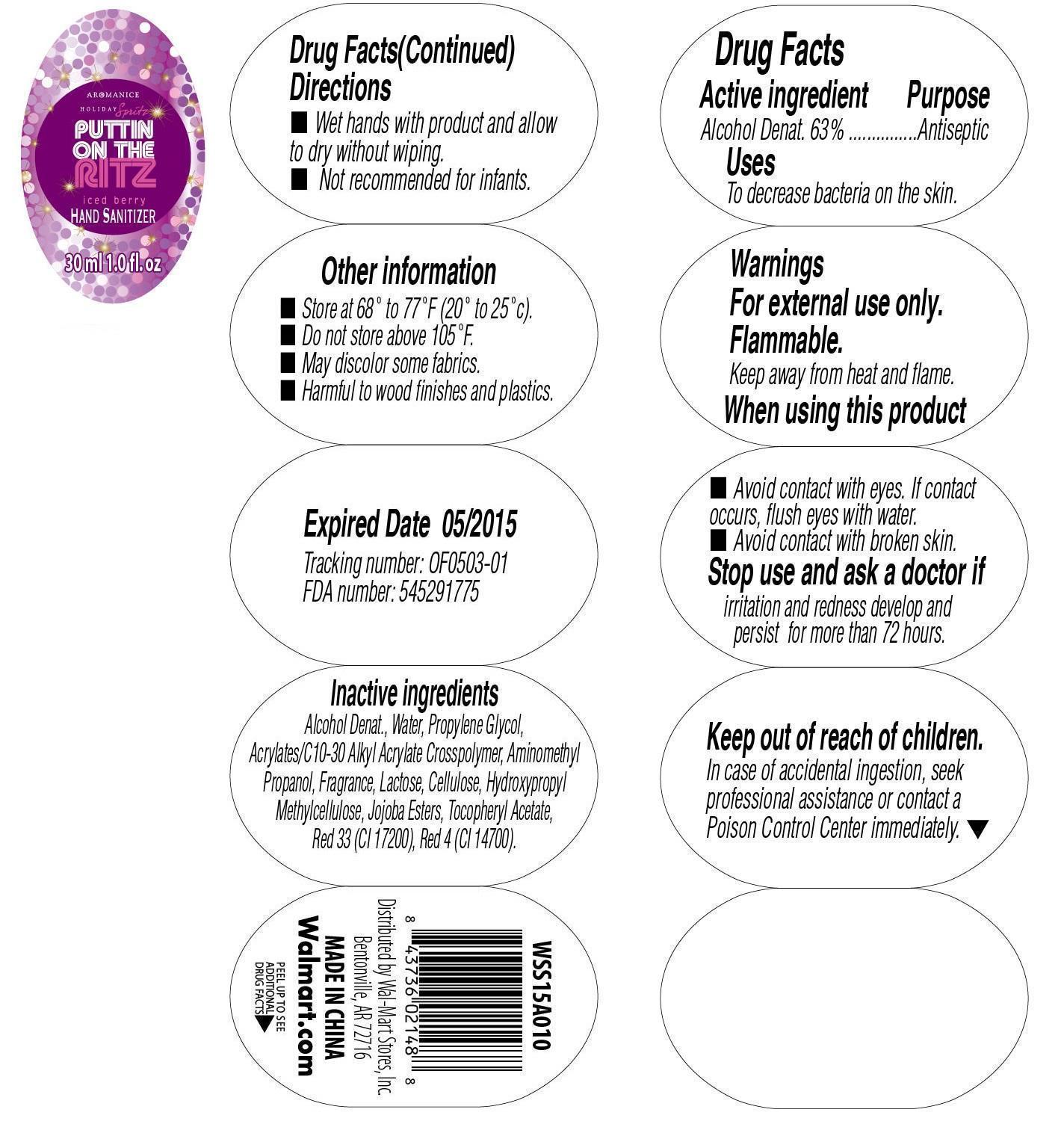 DRUG LABEL: Glitter Ritz Iced Berry
NDC: 49035-233 | Form: GEL
Manufacturer: Wal-Mart Stores Inc.
Category: otc | Type: HUMAN OTC DRUG LABEL
Date: 20150417

ACTIVE INGREDIENTS: ALCOHOL 63 1/100 g
INACTIVE INGREDIENTS: WATER; PROPYLENE GLYCOL; (C10-C30)ALKYL METHACRYLATE ESTER; AMINOMETHYL PROPANEDIOL; LACTOSE; POWDERED CELLULOSE; HYPROMELLOSES; HYDROLYZED JOJOBA ESTERS (ACID FORM); .ALPHA.-TOCOPHEROL ACETATE; FD&C YELLOW NO. 5; FD&C RED NO. 4

Active Ingredient Purpose

Alcohol denat. 63% .................................. Antiseptic

Uses

to decrease bacteria on the skin

Keep out of reach of children. In case of accidental ingestion, seek professional assistance or contact a Poison Control Center immediately.

INDICATIONS AND USAGE

Hand Sanitizer

30 ml 1.0 fl.oz.

Warnings

For external use only.

Flammable.

Keep away from heat and flame.

When using this product

- Avoid contact with eyes. If contact occurs, flush eyes with water.
- Avoid contact with broken skin.

Stop use and ask a doctor if

irritation and redness develop and persist for more than 72 hours.

Directions

- Wet hands with product and allow to dry without wiping.
- Not recommended for infants.

Inactive Ingredients

alcohol denat., water, propylene glycol, acrylates/c10-30 alkyl acrylate crosspolymer, aminomethyl propanol, fragrance, lactose, cellulose, hydroxypropyl methylcellulose, jojoba esters, tocopheryl acetate, yellow 5 (CI 19140), red 4 (CI 14700)